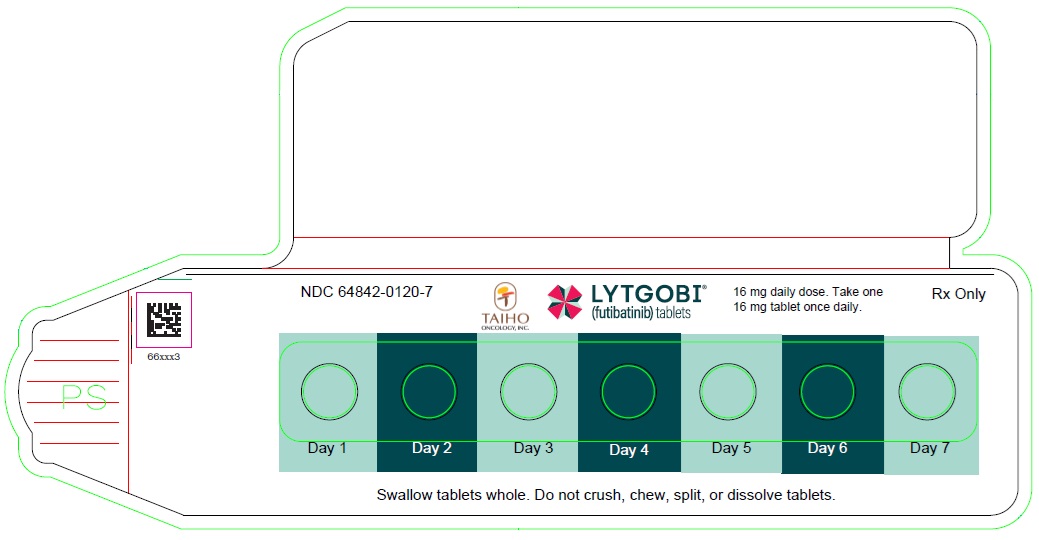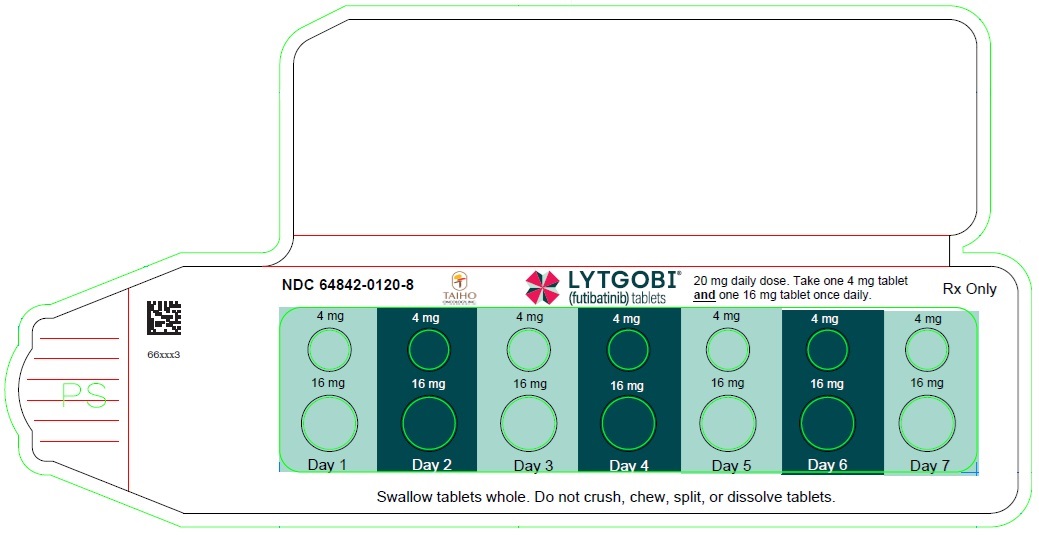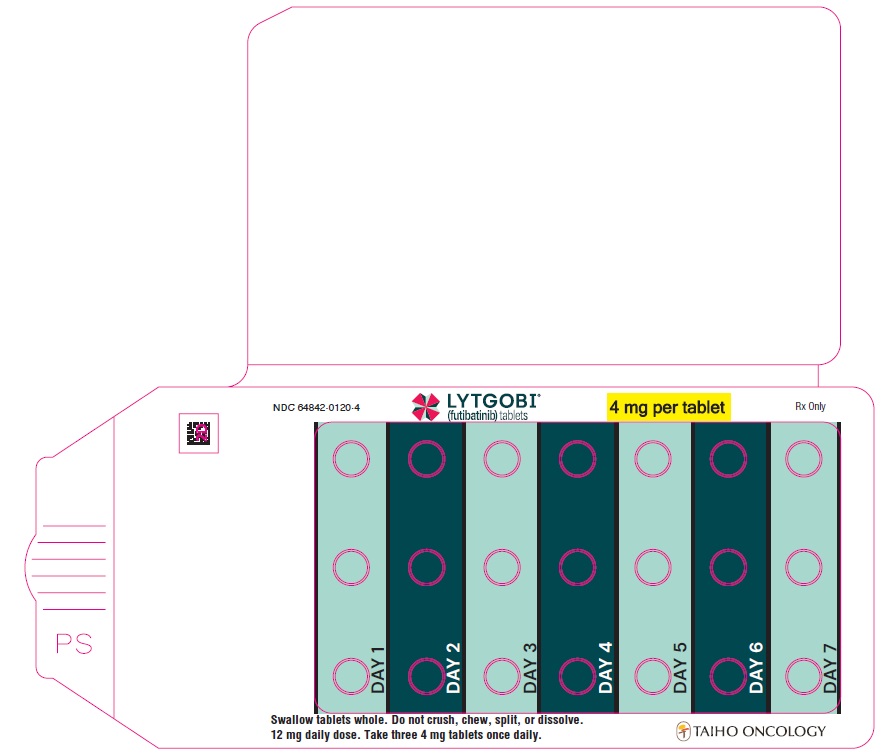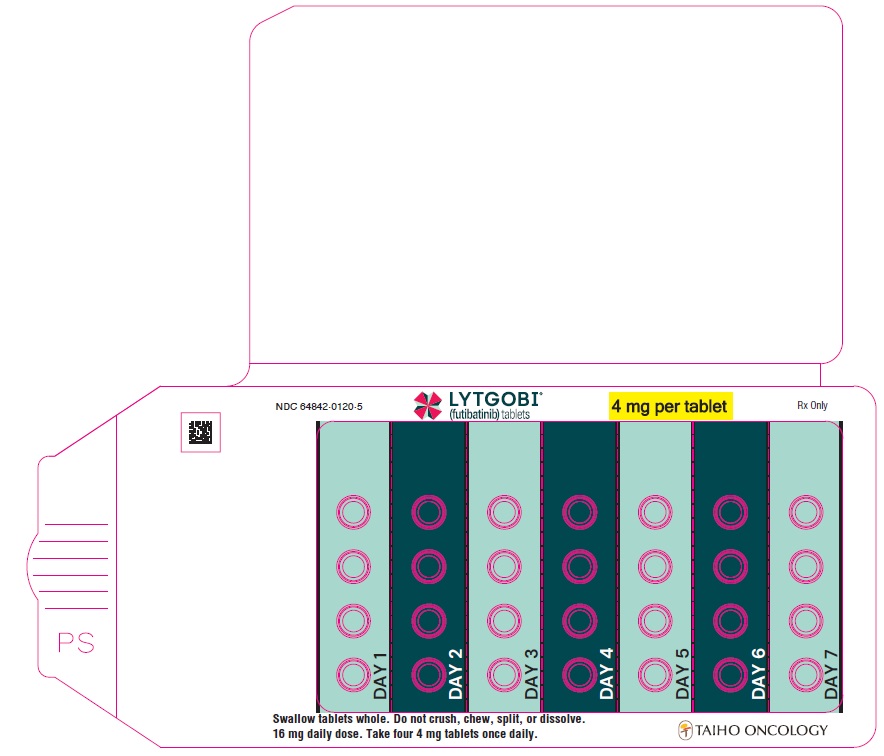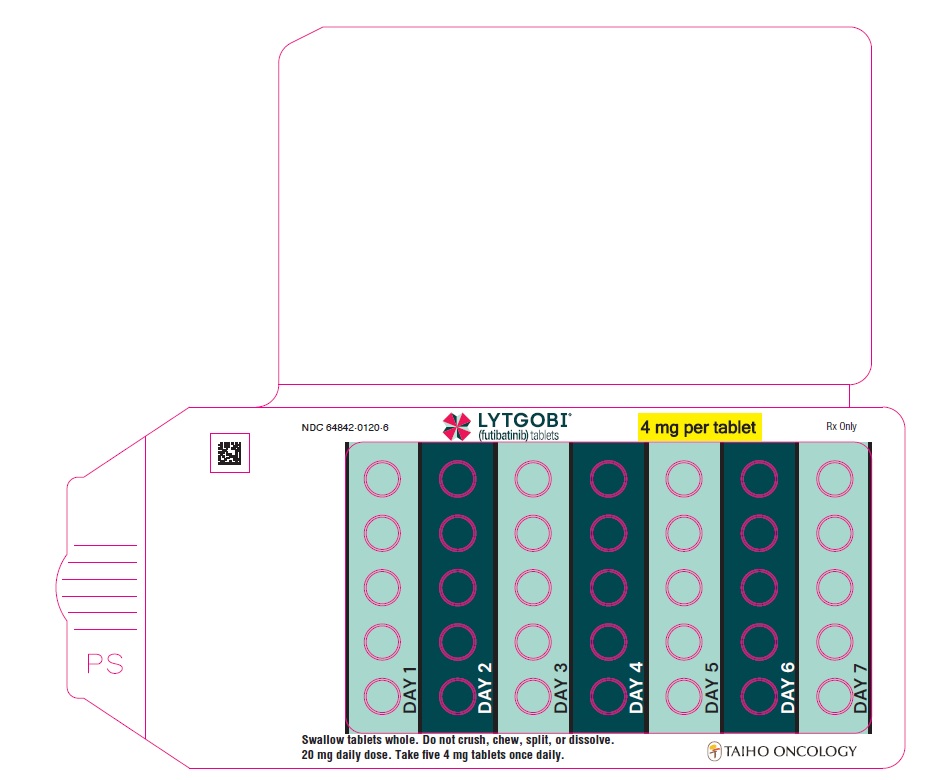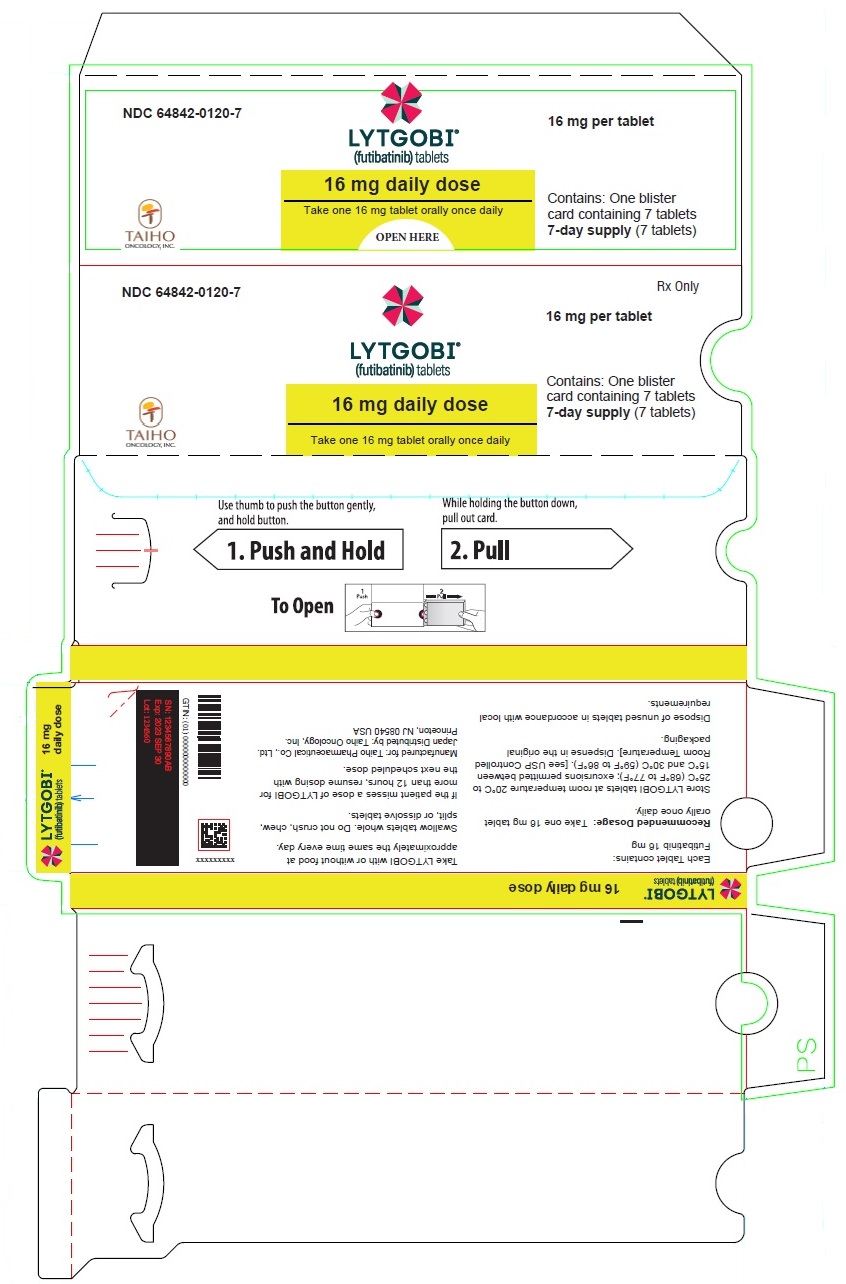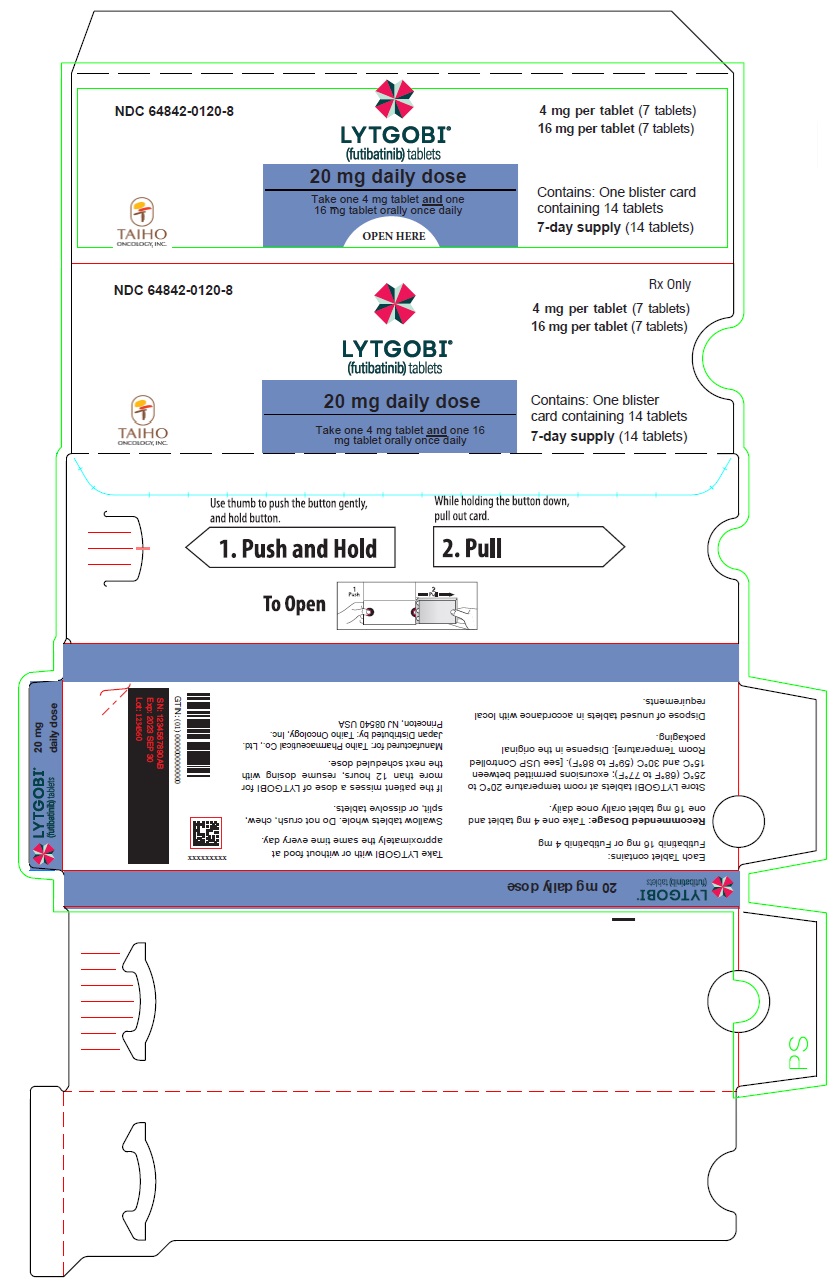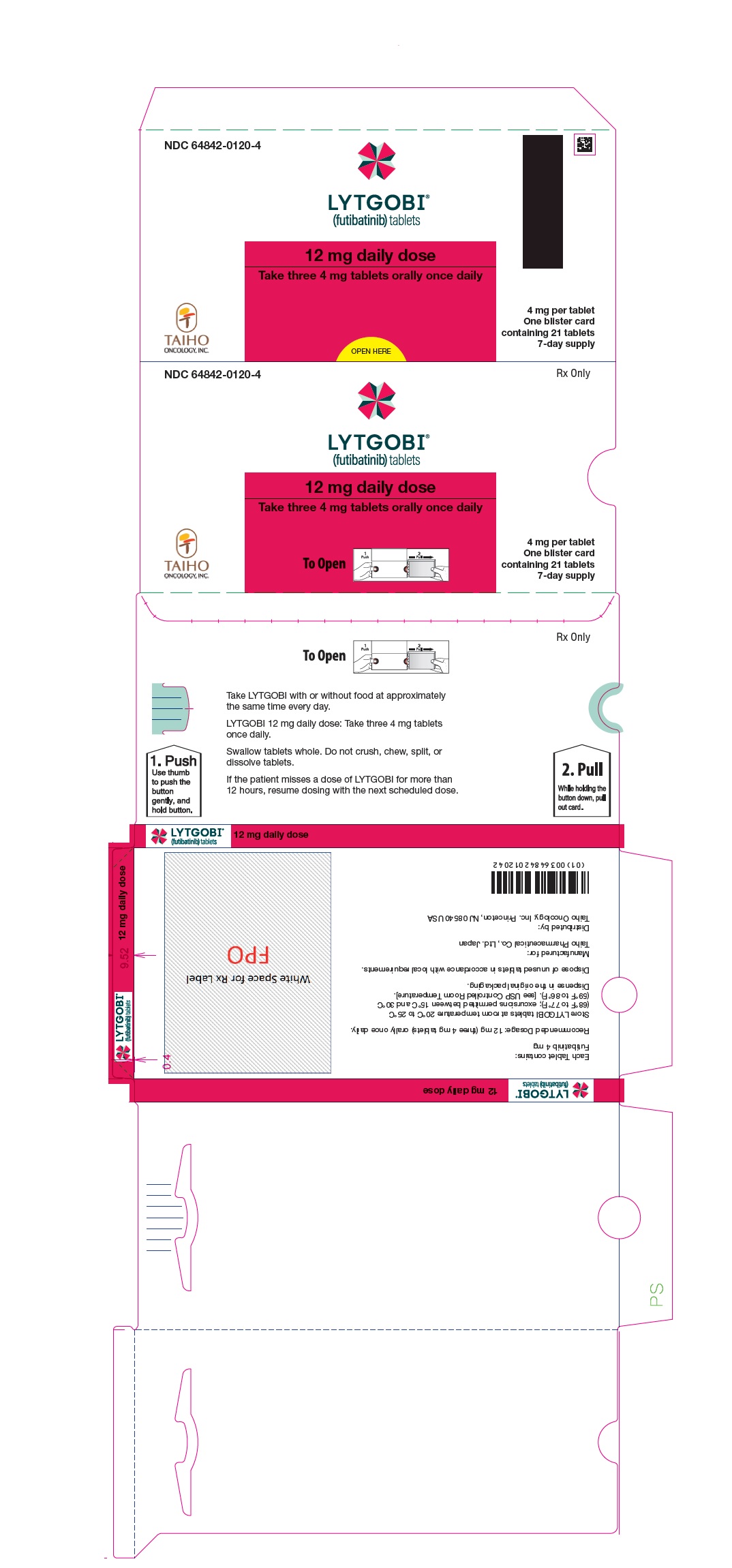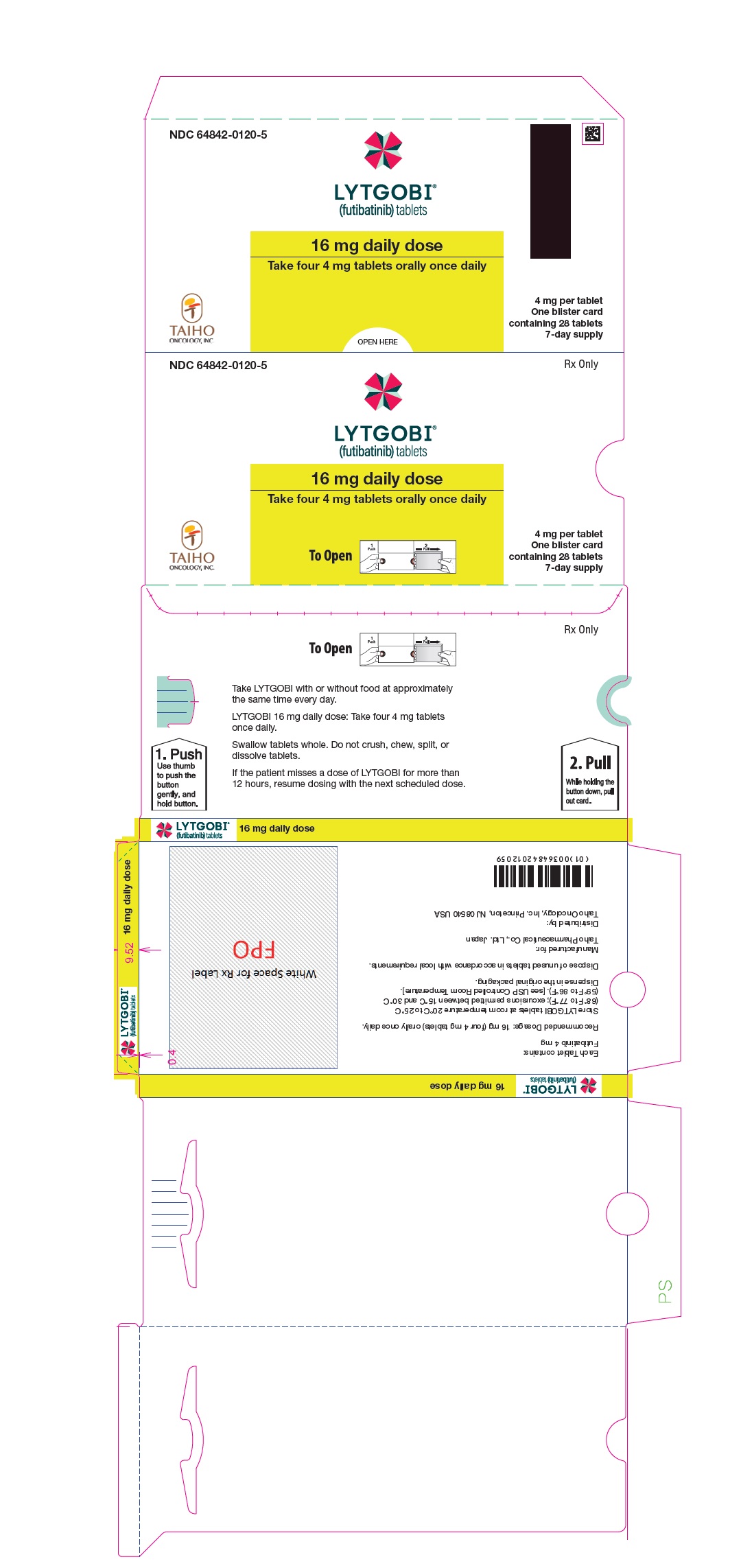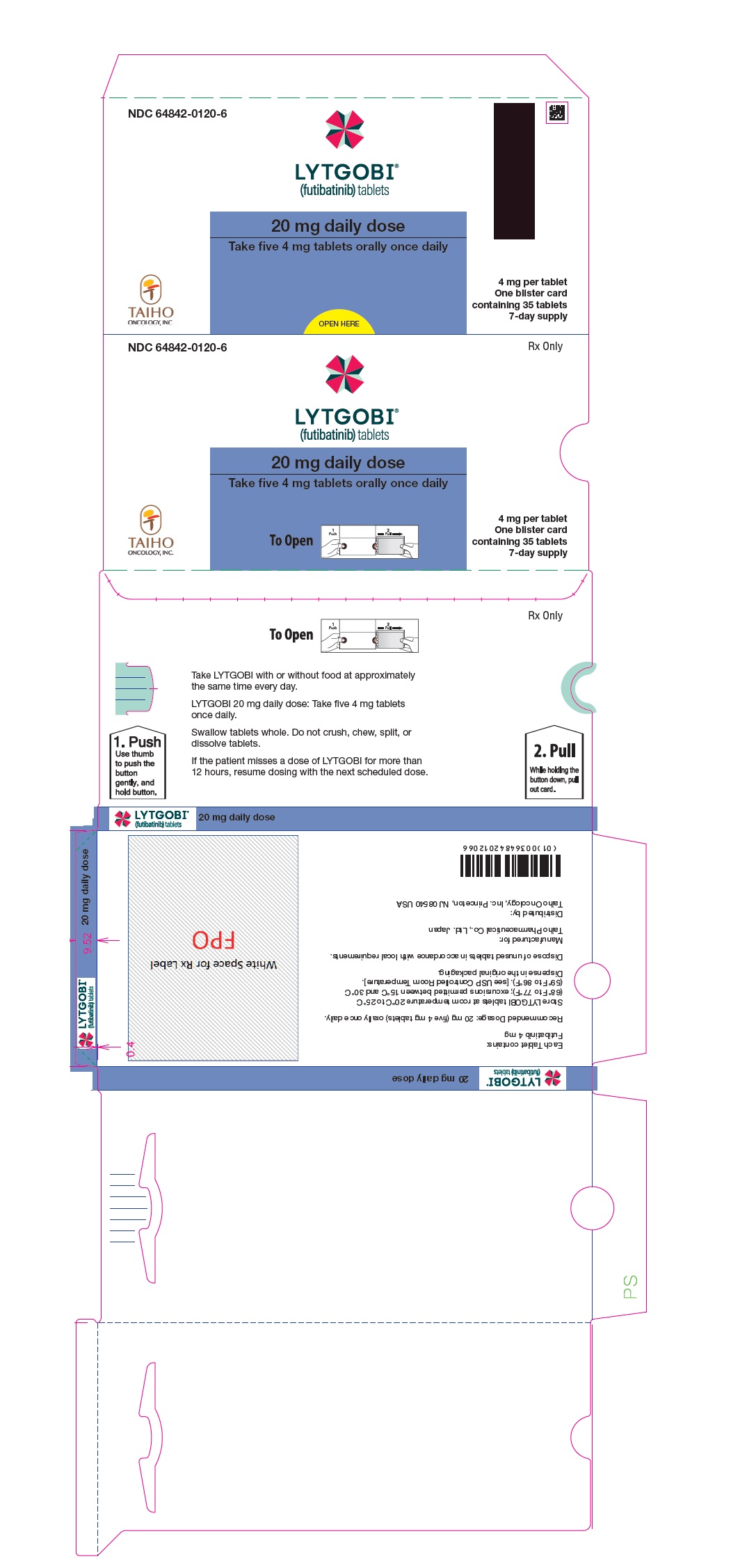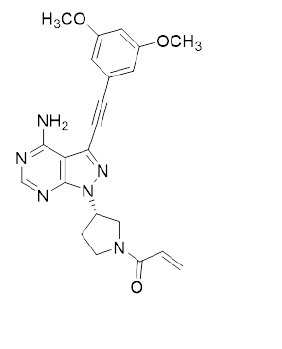 DRUG LABEL: LYTGOBI
NDC: 64842-0120 | Form: TABLET
Manufacturer: TAIHO PHARMACEUTICAL CO., LTD.
Category: prescription | Type: HUMAN PRESCRIPTION DRUG LABEL
Date: 20250731

ACTIVE INGREDIENTS: FUTIBATINIB 4 mg/1 1
INACTIVE INGREDIENTS: STARCH, CORN; CROSPOVIDONE, UNSPECIFIED; HYDROXYPROPYL CELLULOSE, UNSPECIFIED; LACTOSE MONOHYDRATE; MAGNESIUM STEARATE; MANNITOL; MICROCRYSTALLINE CELLULOSE; SODIUM LAURYL SULFATE; HYPROMELLOSE, UNSPECIFIED; POLYETHYLENE GLYCOL, UNSPECIFIED; TITANIUM DIOXIDE

HIGHLIGHTS OF PRESCRIBING INFORMATION

These highlights do not include all the information needed to use LYTGOBI safely and effectively. See full prescribing information for LYTGOBI.
LYTGOBI® (futibatinib) tablets, for oral use
Initial U.S. Approval: 2022

1 INDICATIONS AND USAGE

LYTGOBI is a kinase inhibitor indicated for the treatment of adult patients with previously treated, unresectable, locally advanced or metastatic intrahepatic cholangiocarcinoma harboring fibroblast growth factor receptor 2 (FGFR2) gene fusions or other rearrangements. (1, 2.1)

This indication is approved under accelerated approval based on overall response rate and duration of response. Continued approval for this indication may be contingent upon verification and description of clinical benefit in a confirmatory trial(s). (1)

2 DOSAGE AND ADMINISTRATION

- Confirm the presence of an FGFR2 gene fusion or other rearrangement prior to initiation of treatment with LYTGOBI. (2.1)
- Recommended dose is 20 mg orally (five 4 mg tablets or one 16 mg tablet and one 4 mg tablet) once daily until disease progression or unacceptable toxicity occurs. (2.2)
- Swallow tablet whole, with or without food. (2.2)

3 DOSAGE FORMS AND STRENGTHS

Tablets: 4 mg and 16 mg (3)

4 CONTRAINDICATIONS

None (4)

5 WARNINGS AND PRECAUTIONS

- Ocular Toxicity: LYTGOBI can cause retinal pigment epithelial detachment (RPED). Perform a comprehensive ophthalmological examination including optical coherence tomography (OCT) prior to initiation of therapy, every 2 months for the first 6 months, and every 3 months thereafter and urgently at any time for visual symptoms. (2.3, 5.1)
- Hyperphosphatemia and Soft Tissue Mineralization: Increases in phosphate levels can cause hyperphosphatemia leading to soft tissue mineralization, calcinosis, nonuremic calciphylaxis and vascular calcification. Monitor for hyperphosphatemia and withhold, reduce the dose, or permanently discontinue based on duration and severity of hyperphosphatemia. (2.3, 5.2)
- Embryo-Fetal Toxicity: Can cause fetal harm. Advise patients of reproductive potential of the potential risk to the fetus and to use effective contraception. (5.3, 8.1, 8.3)

6 ADVERSE REACTIONS

- Most common (≥20%) adverse reactions were nail toxicity, musculoskeletal pain, constipation, diarrhea, fatigue, dry mouth, alopecia, stomatitis, abdominal pain, dry skin, arthralgia, dysgeusia, dry eye, nausea, decreased appetite, urinary tract infection, palmar-plantar erythrodysesthesia syndrome, and vomiting. (6.1)
- Most common laboratory abnormalities (≥20%) were increased phosphate, increased creatinine, decreased hemoglobin, increased glucose, increased calcium, decreased sodium, decreased phosphate, increased alanine aminotransferase, increased alkaline phosphatase, decreased lymphocytes, increased aspartate aminotransferase, decreased platelets, increased activated partial thromboplastin time, decreased leukocytes, decreased albumin, decreased neutrophils, increased creatine kinase, increased bilirubin, decreased glucose, increased prothrombin international normalized ratio, and decreased potassium. (6.1)

To report SUSPECTED ADVERSE REACTIONS, contact Taiho Oncology Inc. at 1-844-878-2446 or FDA at 1-800-FDA-1088 or http://www.fda.gov/medwatch.

7 DRUG INTERACTIONS

- Dual P-gp and strong CYP3A inhibitors: Avoid coadministration. (7.1)
- Dual P-gp and strong CYP3A inducers: Avoid coadministration. (7.1)

8 USE IN SPECIFIC POPULATIONS

- Lactation: Advise not to breastfeed. (8.2)

FULL PRESCRIBING INFORMATION

1 INDICATIONS AND USAGE

LYTGOBI is indicated for the treatment of adult patients with previously treated, unresectable, locally advanced or metastatic intrahepatic cholangiocarcinoma harboring fibroblast growth factor receptor 2 (FGFR2) gene fusions or other rearrangements [see Dosage and Administration (2.1)].

This indication is approved under accelerated approval based on overall response rate and duration of response [see Clinical Studies (14.1)]. Continued approval for this indication may be contingent upon verification and description of clinical benefit in a confirmatory trial(s).

2 DOSAGE AND ADMINISTRATION

2.1 Patient Selection

Select patients for the treatment of unresectable, locally advanced or metastatic intrahepatic cholangiocarcinoma with LYTGOBI based on the presence of an FGFR2 gene fusion or rearrangement [see Clinical Studies (14.1)]. An FDA-approved test for detection of FGFR2 gene fusions or other rearrangements in patients with unresectable, locally advanced, or metastatic intrahepatic cholangiocarcinoma for selecting patients for treatment with LYTGOBI is not available.

2.2 Recommended Dosage

The recommended dosage of LYTGOBI is 20 mg (five 4 mg tablets or one 16 mg and one 4 mg tablet) taken orally once daily until disease progression or unacceptable toxicity occurs.

Take LYTGOBI with or without food at approximately the same time each day [see Clinical Pharmacology (12.3)].

Swallow tablets whole. Do not crush, chew, split, or dissolve tablets.

If the patient misses a dose of LYTGOBI for more than 12 hours or if vomiting occurs, resume dosing with the next scheduled dose.

2.3 Dosage Modification for Adverse Reactions

The recommended dose reductions for adverse reactions are provided in Table 1.

Table 1: Recommended Dose Reductions for LYTGOBI for Adverse Reactions
Dose Reduction | Recommended Dosage
First dose reduction | 16 mg (four 4 mg tablets or one 16 mg tablet) orally once daily
Second dose reduction [Permanently discontinue LYTGOBI if unable to tolerate 12 mg orally once daily.] | 12 mg (three 4 mg tablets) orally once daily

Recommended dosage modifications for adverse reactions are provided in Table 2.

Table 2: Recommended Dosage Modifications for LYTGOBI Adverse Reactions
Adverse Reaction | Severity | LYTGOBI Dosage Modifications
Retinal Pigment Epithelial Detachment (RPED) [see Warnings and Precautions (5.1)] | Not applicable | Continue LYTGOBI at the current dose and continue periodic ophthalmic evaluation:; - If resolving within 14 days, continue LYTGOBI at the current dose. - If not resolving within 14 days, withhold LYTGOBI until resolving; then resume LYTGOBI at previous or a lower dose.
Hyperphosphatemia [see Warnings and Precautions (5.2)] | Serum phosphate ≥5.5 - ≤7 mg/dL | Continue LYTGOBI at the current dose and initiate phosphate lowering therapy. Monitor serum phosphate weekly.
Hyperphosphatemia [see Warnings and Precautions (5.2)] | Serum phosphate >7 - ≤10 mg/dL | - Initiate or adjust phosphate lowering therapy. Monitor serum phosphate weekly and - Dose reduce LYTGOBI to next lower dose - If the serum phosphate resolves to ≤7 mg/dL within 2 weeks after dose reduction, continue at this reduced dose. - If serum phosphate is not ≤7 mg/dL within 2 weeks, further reduce LYTGOBI to the next lower dose. - If serum phosphate is not ≤7 mg/dL within 2 weeks after the second dose reduction, withhold LYTGOBI until serum phosphate is ≤7 mg/dL and resume at the dose prior to suspending.
Hyperphosphatemia [see Warnings and Precautions (5.2)] | Serum phosphate >10 mg/dL | - Initiate or adjust phosphate lowering therapy and monitor serum phosphate weekly and - Withhold LYTGOBI until phosphate is ≤7 mg/dL and resume LYTGOBI at the next lower dose. - Permanently discontinue LYTGOBI if serum phosphate is not ≤7 mg/dL within 2 weeks following 2 dose interruptions and reductions.
Other Adverse Reactions | Grade 3a | - Withhold LYTGOBI until toxicity resolves to Grade 1 or baseline, then resume LYTGOBI - for hematological toxicities resolving within 1 week, at the dose prior to suspending. - for other adverse reactions, at next lower dose.
Other Adverse Reactions | Grade 4a | Permanently discontinue LYTGOBI
a Severity as defined by National Cancer Institute Common Terminology Criteria for Adverse Events (NCI CTCAE version 4.03).

3 DOSAGE FORMS AND STRENGTHS

Tablets:

4 mg, round, white, film-coated tablets debossed with “4MG” on one side, and “FBN” on the other side.

16 mg, round, white, film-coated tablets debossed with "16MG" on one side and "FBN" on the other side

4 CONTRAINDICATIONS

None.

5 WARNINGS AND PRECAUTIONS

5.1 Ocular Toxicity

Retinal Pigment Epithelial Detachment (RPED)

LYTGOBI can cause RPED, which may cause symptoms such as blurred vision.

Among 318 patients who received LYTGOBI across clinical trials [see Adverse Reactions (6.1)] where ophthalmologic monitoring did not routinely include optical coherence tomography (OCT), RPED occurred in 9% of patients. The median time to first onset of RPED was 40 days. RPED led to dose interruption of LYTGOBI in 1.3% of patients, dose reduction in 1.6% of patients, and permanent discontinuation in 0.3% of patients.

Perform a comprehensive ophthalmological examination, including OCT of the macula, prior to initiation of therapy, every 2 months for the first 6 months, and every 3 months thereafter. For onset of visual symptoms, refer patients for ophthalmologic evaluation urgently, with follow-up every 3 weeks until resolution or discontinuation of LYTGOBI.

Withhold or reduce the dose of LYTGOBI as recommended [see Dosage and Administration (2.3)].

Dry Eye/Corneal Keratitis

Among 318 patients who received LYTGOBI across clinical trials [see Adverse Reactions (6.1)], dry eye occurred in 15% of patients. Treat patients with ocular demulcents as needed.

5.2 Hyperphosphatemia and Soft Tissue Mineralization

LYTGOBI can cause hyperphosphatemia leading to soft tissue mineralization, calcinosis, nonuremic calciphylaxis, and vascular calcification. Increases in phosphate levels are a pharmacodynamic effect of LYTGOBI [see Clinical Pharmacology (12.2)]. Among 318 patients who received LYTGOBI across clinical trials [see Adverse Reactions (6.1)], hyperphosphatemia was reported in 88% of patients based on laboratory values above the upper limit of normal. The median time to onset of hyperphosphatemia was 5 days (range 3-117). Phosphate binders were received by 77% of patients who received LYTGOBI.

Monitor for hyperphosphatemia throughout treatment. Initiate a low phosphate diet and phosphate lowering therapy when serum phosphate level is ≥5.5 mg/dL. For serum phosphate levels >7 mg/dL, initiate or intensify phosphate lowering therapy and dose reduce, withhold, or permanently discontinue LYTGOBI based on duration and severity of hyperphosphatemia [see Dosage and Administration (2.3)].

5.3 Embryo-Fetal Toxicity

Based on findings in an animal study and its mechanism of action, LYTGOBI can cause fetal harm when administered to a pregnant woman. Oral administration of futibatinib to pregnant rats during the period of organogenesis caused fetal malformations, fetal growth retardation, and embryo-fetal death at maternal exposures lower than the human exposure at the clinical dose of 20 mg based on area under the curve (AUC).

Advise pregnant women of the potential risk to the fetus. Advise female patients of reproductive potential to use effective contraception during treatment with LYTGOBI and for 1 week after the last dose of LYTGOBI. Advise males with female partners of reproductive potential to use effective contraception during treatment with LYTGOBI and for 1 week after the last dose [see Use in Specific Populations (8.1, 8.3)].

6 ADVERSE REACTIONS

The following adverse reactions are discussed elsewhere in the labeling:

- Ocular Toxicity [see Warnings and Precautions (5.1)]
- Hyperphosphatemia and Soft Tissue Mineralization [see Warnings and Precautions (5.2)]

6.1 Clinical Trials Experience

Because clinical trials are conducted under widely varying conditions, adverse reaction rates observed in the clinical trials of a drug cannot be directly compared to rates in the clinical trials of another drug and may not reflect the rates observed in practice.

The pooled safety population described in the WARNINGS AND PRECAUTIONS reflect exposure to LYTGOBI as a single agent at 20 mg orally once daily in 318 patients including 145 patients with cholangiocarcinoma and 173 patients with other advanced solid tumors. Among 318 patients who received LYTGOBI, 37% were exposed for 6 months or longer and 13% were exposed for greater than 12 months.

Previously Treated, Unresectable Locally Advanced or Metastatic Intrahepatic Cholangiocarcinoma

The safety of LYTGOBI was evaluated in Study TAS-120-101, which included 103 patients with previously treated, unresectable locally advanced or metastatic intrahepatic cholangiocarcinoma harboring FGFR2 fusions or other gene rearrangements [see Clinical Studies (14.1)]. Patients were treated with LYTGOBI 20 mg orally once daily until disease progression or unacceptable toxicity. The median duration of treatment was 9 months (range: 0.5 - 25 months).

Serious adverse reactions occurred in 39% of patients receiving LYTGOBI. Serious adverse reactions in ≥2% of patients who received LYTGOBI included pyrexia (3.9%), gastrointestinal hemorrhage (3.9%), ascites (2.9%), musculoskeletal pain (2.9%), and bile duct obstruction (2.9%).

Permanent discontinuation due to an adverse reaction occurred in 4.9% of patients who received LYTGOBI. Adverse reactions requiring permanent discontinuation of LYTGOBI in one patient each were esophagitis, oral dysesthesia, bile duct obstruction, dizziness, and anemia.

Dosage interruptions due to an adverse reaction occurred in 66% of patients who received LYTGOBI. Adverse reactions requiring dosage interruption in ≥5% of patients included hyperphosphatemia, palmar-plantar erythrodysesthesia syndrome, increased alanine aminotransferase, increased aspartate aminotransferase, and fatigue.

Dose reductions due to an adverse reaction occurred in 58% of patients who received LYTGOBI. Adverse reactions requiring dosage reductions in ≥2% of patients who received LYTGOBI included hyperphosphatemia, palmar-plantar erythrodysesthesia syndrome, fatigue, increased alanine aminotransferase, increased aspartate aminotransferase, nail toxicity, and stomatitis.

The most common (≥20%) adverse reactions were nail toxicity, musculoskeletal pain, constipation, diarrhea, fatigue, dry mouth, alopecia, stomatitis, abdominal pain, dry skin, arthralgia, dysgeusia, dry eye, nausea, decreased appetite, urinary tract infection, palmar-plantar erythrodysesthesia syndrome, and vomiting.

The most common laboratory abnormalities (≥20%) were increased phosphate, increased creatinine, decreased hemoglobin, increased glucose, increased calcium, decreased sodium, decreased phosphate, increased alanine aminotransferase, increased alkaline phosphatase, decreased lymphocyte, increased aspartate aminotransferase, decreased platelets, increased activated partial thromboplastin time, decreased leukocytes, decreased albumin, decreased neutrophils, increased creatine kinase, increased bilirubin, decreased glucose, increased prothrombin international normalized ratio, and decreased potassium.

Table 3 summarizes the adverse reactions in TAS-120-101. Table 4 summarizes laboratory abnormalities in TAS-120-101.

Table 3: Adverse Reactions (≥15%) in Patients Receiving LYTGOBI in Study TAS-120-101
 | LYTGOBI N = 103
Adverse Reaction | All Grades a (%) | Grade 3 (%)
Skin and subcutaneous tissue disorders
Nail toxicity b | 47 | 1.9
Alopecia | 34 | 0
Dry skin | 29 | 0
Palmar-plantar erythrodysesthesia syndrome | 21 | 4.9
Gastrointestinal disorders
Constipation | 39 | 0
Diarrhea c | 39 | 1
Dry mouth | 35 | 0
Stomatitis d | 30 | 6
Abdominal pain e | 30 | 2.9
Nausea | 24 | 1.9
Vomiting f | 20 | 1
General disorders
Fatigue g | 37 | 8
Metabolism and nutrition disorders
Decreased appetite | 23 | 2.9
Musculoskeletal and connective tissue disorder
Musculoskeletal pain h | 43 | 3.9
Arthralgia i | 25 | 0
Eye disorders
Dry eye j | 25 | 1
Nervous system disorders
Dysgeusia k | 25 | 0
Infections
Urinary tract infection l | 23 | 2.9
Investigations
Weight decreased | 18 | 3.9
a Graded per NCI CTCAE 4.03.
b Includes nail toxicity, nail disorder, nail discoloration, nail dystrophy, nail hypertrophy, nail infection, nail pigmentation, onychalgia, onychoclasis, onycholysis, onychomadesis, onychomycosis, and paronychia.
c Includes diarrhea, colitis, and gastroenteritis.
d Includes stomatitis, glossitis, mouth ulceration, mucosal inflammation, pharyngeal inflammation, and tongue ulceration.
e Includes abdominal pain, abdominal discomfort, abdominal pain upper, gastrointestinal pain, and hepatic pain.
f Includes vomiting and hematemesis.
g Includes fatigue and asthenia.
h Includes back pain, bone pain, musculoskeletal chest pain, musculoskeletal discomfort, musculoskeletal pain, musculoskeletal stiffness, myalgia, neck pain, non-cardiac chest pain, pain in extremity, and spinal pain.
i Includes arthralgia and arthritis.
j Includes dry eye, keratitis, lacrimation increased, photokeratitis, punctate keratitis, and ulcerative keratitis.
k Includes dysgeusia, ageusia, and taste disorder.
l Includes urinary tract infection, cystitis, and dysuria.

Clinically relevant adverse reactions occurring in ≤15% of patients included retinal pigment epithelial detachment (RPED, 7.8%).

Table 4: Select Laboratory Abnormalities (≥10%) Worsening from Baseline in Patients Receiving LYTGOBI in TAS-120-101
 | LYTGOBI N = 103
Laboratory Abnormality a | All Grades b (%) | Grades 3 or 4 (%)
Hematology
Decreased hemoglobin | 52 | 6
Decreased lymphocytes | 46 | 10
Decreased platelets | 42 | 1
Decreased leukocytes | 33 | 1.1
Decreased neutrophils | 31 | 1.6
Chemistry
Increased phosphate c | 97 | 39
Increased creatinine d | 58 | 0
Increased glucose | 52 | 4.9
Increased calcium | 51 | 1.2
Decreased sodium | 51 | 15
Decreased phosphate | 50 | 20
Increased alanine aminotransferase | 50 | 7
Increased alkaline phosphatase | 47 | 4.9
Increased aspartate aminotransferase | 46 | 13
Decreased albumin | 31 | 2.4
Increased creatine kinase | 31 | 5
Increased bilirubin | 28 | 0
Decreased glucose | 25 | 0
Decreased potassium | 22 | 2.1
Increased potassium | 16 | 2
Coagulation
Increased activated partial thromboplastin time | 36 | 8
Increased prothrombin international normalized ratio | 25 | 0
a Graded per NCI CTCAE 4.03.
b Percentages are based on patients with data at both baseline and at least one post-baseline data value.
c NCI CTCAE 4.03 does not define grades for increased phosphate. Laboratory value shift table categories were used to assess increased phosphorus levels (Grades ≥3 defined as >7 mg/dL).
d Graded based on comparison to upper limit of normal.

7 DRUG INTERACTIONS

7.1 Effect of Other Drugs on LYTGOBI

Futibatinib is a substrate of CYP3A and P-gp.

Dual P-gp and Strong CYP3A Inhibitors

Avoid concomitant use of drugs that are dual P-gp and strong CYP3A inhibitors with LYTGOBI.

Concomitant use of drugs that are dual P-gp and strong CYP3A inhibitors with LYTGOBI may increase futibatinib exposure [see Clinical Pharmacology (12.3)], which may increase the incidence and severity of adverse reactions.

Dual P-gp and Strong CYP3A Inducers

Avoid concomitant use of dual P-gp and strong CYP3A inducers with LYTGOBI.

Concomitant use of drugs that are dual P-gp and strong CYP3A inducers may decrease futibatinib exposure [see Clinical Pharmacology (12.3)], which may reduce the efficacy of LYTGOBI.

7.2 Effect of LYTGOBI on Other Drugs

Futibatinib is an inhibitor of P-gp and BCRP.

P-gp or BCRP Substrates:

Consider more frequent monitoring for adverse reactions associated with concomitantly administered drugs that are sensitive substrates of P-gp or BCRP and reduce the dose of these drugs per their Prescribing Information.

Futibatinib may increase exposure of drugs that are substrates of P-gp or BCRP [see Clinical Pharmacology (12.3)].

8 USE IN SPECIFIC POPULATIONS

8.1 Pregnancy

Risk Summary

Based on findings in an animal study and its mechanism of action, LYTGOBI can cause fetal harm or loss of pregnancy when administered to a pregnant woman [see Clinical Pharmacology (12.1)]. There are no available data on the use of LYTGOBI in pregnant women. Oral administration of futibatinib to pregnant rats during the period of organogenesis at maternal plasma exposures below the human exposure at the clinical dose of 20 mg resulted in fetal malformations, fetal growth retardation, and embryo-fetal death (see Data). Advise pregnant women of the potential risk to a fetus.

In the U.S. general population, the estimated background risk of major birth defects and miscarriage in clinically recognized pregnancies is 2% to 4% and 15% to 20%, respectively.

Data

Animal Data

Once daily oral administration of futibatinib to pregnant rats during the period of organogenesis resulted in 100% embryofetal mortality due to post-implantation loss at doses ≥10 mg/kg (approximately 5 times the recommended clinical dose of 20 mg based on body surface area, BSA). Fetal survival was unaffected at 0.5 mg/kg per day; however, once daily oral administration of futibatinib at the 0.5 mg/kg dose level (approximately 0.2 times the recommended clinical dose of 20 mg based on BSA) resulted in reduced mean fetal body weight and an increase in fetal skeletal and visceral malformations, major blood vessel variations, and reduced ossification.

8.2 Lactation

Risk Summary

There are no data on the presence of futibatinib or its metabolites in human milk or their effects on either the breastfed child or on milk production. Because of the potential for serious adverse reactions from LYTGOBI in breastfed children, advise women not to breastfeed during treatment and for 1 week after the last dose.

8.3 Females and Males of Reproductive Potential

LYTGOBI can cause fetal harm when administered to a pregnant woman [see Use in Specific Populations (8.1)].

Pregnancy Testing

Verify pregnancy status of females of reproductive potential prior to initiating LYTGOBI [see Use in Specific Populations (8.1)].

Contraception

Females

Advise females of reproductive potential to use effective contraception during treatment with LYTGOBI and for 1 week after the last dose.

Males

Advise males with female partners of reproductive potential or who are pregnant to use effective contraception during treatment with LYTGOBI and for 1 week after the last dose.

8.4 Pediatric Use

The safety and effectiveness of LYTGOBI have not been established in pediatric patients.

Animal Toxicity Data

In 4- or 13-week repeat-dose toxicology studies in adult rats and dogs, findings included increased inorganic phosphorus and calcium in plasma, ectopic mineralization in various organs and tissues, and lesions in bone/cartilage at futibatinib exposures lower than the human exposure at the clinical dose of 20 mg. Findings in rats also included corneal lesions. Evidence of recovery in rats and dogs was observed four weeks after cessation of dosing except for the ectopic mineralization.

8.5 Geriatric Use

Of the 103 patients treated with LYTGOBI in Study TAS-120-101, 22% were 65 years or older. Based on available data, no overall differences in safety or effectiveness of LYTGOBI have been observed between patients 65 years of age and older and younger adult patients.

8.7 Hepatic Impairment

There are limited data in patients treated with LYTGOBI with total bilirubin >1.5 × ULN, and patients with cholangiocarcinoma with total bilirubin >3 × ULN were excluded from enrollment in clinical trials. Patients with cirrhosis and total bilirubin >1.5 × ULN to 3 × ULN may have the potential for increased adverse reactions compared to patients with normal hepatic function due to higher unbound futibatinib exposure [see Clinical Pharmacology (12.3)].

11 DESCRIPTION

Futibatinib is a kinase inhibitor with the chemical name 1-[(3S)-3-{4-amino-3-[(3,5-dimethoxyphenyl)ethynyl]- 1H-pyrazolo[3,4-d]pyrimidin-1-yl}pyrrolidin-1-yl]prop-2-en-1-one. Futibatinib has a molecular formula of C22H22N6O3 and molecular mass of 418.45 g/mole. Futibatinib has the following chemical structure:

Futibatinib is a white crystalline powder. The solubility of futibatinib is pH dependent with decreasing solubility with increasing pH, being practically insoluble at pH 3 or higher. Futibatinib is insoluble in water and poorly soluble in common solvents. LYTGOBI is supplied as 4 mg and 16 mg film-coated tablets for oral administration. Each tablet contains inactive ingredients of corn starch, crospovidone, hydroxypropyl cellulose, lactose monohydrate, magnesium stearate, mannitol, microcrystalline cellulose, and sodium lauryl sulfate. The film coating material contains hypromellose, magnesium stearate, polyethylene glycol, and titanium dioxide.

12 CLINICAL PHARMACOLOGY

12.1 Mechanism of Action

Futibatinib is a small molecule kinase inhibitor of FGFR 1, 2, 3, and 4 with IC50 values of less than 4 nM. Futibatinib covalently binds FGFR. Constitutive FGFR signaling can support the proliferation and survival of malignant cells. Futibatinib inhibited FGFR phosphorylation and downstream signaling and decreased cell viability in cancer cell lines with FGFR alterations including FGFR fusions/rearrangements, amplifications, and mutations. Futibatinib demonstrated anti-tumor activity in mouse and rat xenograft models of human tumors with activating FGFR genetic alterations.

12.2 Pharmacodynamics

Serum Phosphate

Futibatinib increased serum phosphate levels due to FGFR inhibition. Serum phosphate increased with increasing futibatinib exposure across the dose range of 4 to 24 mg orally once daily (0.2 to 1.2 times the recommended dose), with increased risk of hyperphosphatemia at higher futibatinib exposure.

Cardiac Electrophysiology

At four times the approved recommended dose, LYTGOBI does not cause clinically significant QTc interval prolongation.

12.3 Pharmacokinetics

The pharmacokinetics of futibatinib administered 20 mg once daily were evaluated in patients with advanced solid tumors unless otherwise specified.

Futibatinib exposure (AUC) increased proportionally over the dose range from 4 to 24 mg orally once daily (0.2 to 1.2 times the maximum approved recommended dosage). At the recommended dosage, the geometric mean (coefficient of variation [CV] %) maximal concentration of futibatinib at steady state (Cmax,ss) was 144 ng/mL (50%) and AUC at steady state (AUCss) was 790 ng∙hr/mL (45%), with no accumulation after repeat doses.

Absorption

Median time to reach maximum futibatinib plasma concentration (Tmax) was 2 (range: 1.2 to 22.8) hours.

Effect of Food

Administration of LYTGOBI with a high-fat and high-calorie meal (900 to 1000 calories with approximately 50% of total caloric content from fat) decreased futibatinib AUC by 11% and Cmax by 42% in healthy subjects.

Distribution

The geometric mean (CV%) apparent volume of distribution (Vc/F) is 66 L (18%). Futibatinib is 95% bound to human plasma protein at 0.2 to 5 µmol/L in vitro, primarily to albumin and α1-acid glycoprotein.

Elimination

The mean (CV%) elimination half-life (T½) of futibatinib is 2.9 hours (27%) and the geometric mean (CV%) apparent clearance (CL/F) is 20 L/h (23%).

Metabolism

Futibatinib is primarily metabolized by CYP3A and to a lesser extent by CYP2C9 and CYP2D6 in vitro. Unchanged futibatinib is the major drug-related moiety in plasma (59% of radioactivity) in healthy subjects.

Excretion

Following a single oral dose of 20 mg radiolabeled futibatinib, approximately 91% of the total recovered radioactivity was observed in feces and 9% in urine, with negligible unchanged futibatinib in urine or feces.

Specific Populations

No clinically meaningful differences in the systemic exposure of futibatinib were observed based on age (18 - 82 years), sex, race (White, Asian, and African American), body weight (36 - 152 kg), or mild to moderate renal impairment (creatinine clearance [CLcr] 30 - 89 mL/min estimated by Cockcroft-Gault).

The pharmacokinetics of futibatinib has not been studied in patients with severe renal impairment (CLcr 15 - 29 mL/min), renal dialysis in end-stage renal disease (CLcr <15 mL/min), or moderate or severe hepatic impairment (total bilirubin >1.5 × ULN and any AST) without cirrhosis.

Patients with Hepatic Impairment

In subjects with mild hepatic impairment (total bilirubin ≤ upper limit of normal [ULN] and aspartate transaminase [AST] > ULN, or total bilirubin >1 to 1.5 × ULN and any AST, or Child-Pugh A), or moderate to severe hepatic impairment (Child-Pugh B to C) with total bilirubin < 1.5 × ULN, there are no clinically meaningful differences in the systemic exposure of futibatinib.

In subjects with cirrhosis and total bilirubin >1.0 to 1.5 × ULN, mean unbound futibatinib AUC and Cmax increased by 1.7-fold relative to subjects with normal hepatic function. In subjects with cirrhosis and total bilirubin >1.5 × ULN, mean unbound futibatinib AUC and Cmax increased by 3.2-fold and 2.4-fold, respectively, compared to values in healthy subjects.

Drug Interaction Studies

Clinical Studies

Effect of Other Drugs on Futibatinib

Dual P-gp and strong CYP3A inhibitors: Co-administration of multiple doses of itraconazole (P-gp and strong CYP3A inhibitor) increased single dose futibatinib Cmax by 51% and AUC by 41% [see Drug Interactions (7.1)].

Dual P-gp and strong CYP3A inducers: Co-administration of multiple doses of rifampin (P-gp and strong CYP3A inducer) decreased single dose futibatinib Cmax by 53% and AUC by 64% [see Drug Interactions (7.1)].

The effect of a P-gp modulator (without CYP3A modulation), or a strong CYP3A modulator (without P-gp modulation) on the exposure of futibatinib has not been investigated.

Gastric acid reducing agents: Co-administration of multiple doses of lansoprazole (proton pump inhibitor) had no effect on single dose futibatinib AUC.

Effect of Futibatinib On Other Drugs

CYP3A substrates: Co-administration of multiple doses of futibatinib had no effect on single dose midazolam (sensitive CYP3A substrate) AUC.

In Vitro Studies

Effect of Transporters on Futibatinib: Futibatinib is a substrate for P-gp and BCRP, but not for OATP1B1 or OATP1B3.

Effect of Futibatinib on CYP Enzymes: Futibatinib does not inhibit CYP1A2, CYP2B6, CYP2C8, CYP2C9, CYP2C19, CYP2D6 or CYP3A, and does not induce CYP1A2, CYP2B6 or CYP3A4 at clinically relevant concentrations.

Effect of Futibatinib on Transporter Systems: Futibatinib inhibits P-gp and BCRP, but does not inhibit OAT1, OAT3, OCT2, OATP1B1, OATP1B3, MATE1, or MATE2K at clinically relevant concentrations.

13 NONCLINICAL TOXICOLOGY

13.1 Carcinogenesis, Mutagenesis, Impairment of Fertility

Carcinogenicity studies have not been conducted with futibatinib.

Futibatinib was not mutagenic in an in vitro bacterial reverse mutation (Ames) assay. Futibatinib was clastogenic in an in vitro chromosomal aberration assay. Futibatinib was not clastogenic in a rat bone marrow micronucleus assay or a rat DNA damaging (Comet) assay.

Dedicated fertility studies with futibatinib have not been conducted.

14 CLINICAL STUDIES

14.1 Cholangiocarcinoma

TAS-120-101 (NCT02052778), a multicenter, open-label, single-arm trial, evaluated the efficacy of LYTGOBI in 103 patients with previously treated, unresectable, locally advanced or metastatic intrahepatic cholangiocarcinoma. The presence of FGFR2 fusions or other rearrangements was determined in 102 enrolled patients (99%) using next generation sequencing (NGS) testing. Qualifying in-frame fusions and other rearrangements were predicted to have a breakpoint within intron 17/exon 18 of the FGFR2 gene leaving the FGFR2 kinase domain intact.

Patients received LYTGOBI at a dosage of 20 mg orally once daily until disease progression or unacceptable toxicity. The major efficacy outcome measures were overall response rate (ORR) and duration of response (DoR) as determined by an independent review committee (IRC) according to Response Evaluation Criteria in Solid Tumors (RECIST) v1.1.

The trial population characteristics were: Median age was 58 years (range: 22 to 79 years) with 22% of patients ≥65 years, 56% were female, race was: 50% White, 29% Asian, 8% Black or African American, 1% Native Hawaiian or Other Pacific Islander, 13% unknown, baseline Eastern Cooperative Oncology Group (ECOG) performance status of 0 (47%) or 1 (53%). Seventy-eight percent (78%) of patients had in-frame FGFR2 gene fusions and the most commonly identified FGFR2 fusion partner was BICC1 (n=24, 23%). Twenty-two percent (22%) of patients had other FGFR2 rearrangements that may not be in-frame with the partner gene or the partner gene was not identifiable.

All patients had received at least 1 prior systemic therapy, 30% had 2 prior lines of therapy, and 23% had 3 or more prior lines of therapy. All patients received a prior platinum-based therapy including 91% with prior gemcitabine/cisplatin.

Efficacy results are summarized in Table 5. The median time to response was 2.5 months (range 0.7 – 7.4 months).

Table 5: Efficacy Results in TAS-120-101
Efficacy Parameter | LYTGOBI N = 103
ORR (95% CI)a | 42% (32, 52)
Partial response, n (%) | 43 (42%)
Median DoR (months) (95% CI)b | 9.7 (7.6, 17.1)
DoR ≥6 months, n (%) | 31 (72%)
DoR ≥12 months, n (%) | 6 (14%)
a The 95% confidence interval (CI) was calculated using Clopper–Pearson method.
b The 95% confidence interval (CI) was constructed based on a log-log transformed CI for the survival function.

16 HOW SUPPLIED/STORAGE AND HANDLING

LYTGOBI tablets are round, white, and film-coated. The 4 mg tablets are debossed with “4MG” on one side, and “FBN” on the other side. The 16 mg tablets are debossed with “16MG” on one side, and “FBN” on the other. Tablets are packaged in blister cards and supplied in child-resistant DosePak® as follows:

- 20 mg daily dose: Each carton contains 1 blister card containing a 7-day supply (35 tablets; 4 mg futibatinib per tablet). [NDC-64842-0120-6]
- 20 mg daily dose: Each carton contains 1 blister card containing a 7-day supply (14 tablets; 7 tablets each of 4 mg and 16 mg futibatinib per tablet). [NDC-64842-0120-8]
- 16 mg daily dose: Each carton contains 1 blister card containing a 7-day supply (28 tablets; 4 mg futibatinib per tablet). [NDC-64842-0120-5]
- 16 mg daily dose: Each carton contains 1 blister card containing a 7-day supply (7 tablets; 16 mg futibatinib per tablet). [NDC-64842-0120-7]
- 12 mg daily dose: Each carton contains 1 blister card containing a 7-day supply (21 tablets; 4 mg futibatinib per tablet). [NDC-64842-0120-4]

Store LYTGOBI tablets at room temperature 20°C to 25°C (68°F to 77°F); excursions permitted between 15°C and 30°C (59°F to 86°F). ([see USP Controlled Room Temperature]).

17 PATIENT COUNSELING INFORMATION

Advise the patient to read the FDA-approved patient labeling (Patient Information).

Ocular Toxicity

Advise patients that LYTGOBI may cause ocular toxicity including RPED and to immediately inform their healthcare provider if they experience any visual changes [see Warnings and Precautions (5.1)]. Advise patients to use artificial tears, or hydrating or lubricating eye gels to prevent or treat dry eyes [see Warnings and Precautions (5.1)].

Hyperphosphatemia and Soft Tissue Mineralization

Inform patients that LYTGOBI may cause hyperphosphatemia and soft tissue mineralization and to immediately inform their healthcare provider of any symptoms related to acute change in phosphate levels such as muscle cramps, numbness, or tingling around the mouth [see Warnings and Precautions 5.2)].

Nail Disorders

Advise patients that LYTGOBI may cause nail disorders [see Adverse Reactions (6.1)].

Embryo-Fetal Toxicity

- Advise females to inform their healthcare provider if they are pregnant or become pregnant. Inform female patients of the risk to a fetus and potential loss of pregnancy [see Warnings and Precautions (5.3) and Use in Specific Populations (8.1)].
- Advise females of reproductive potential to use effective contraception while on LYTGOBI and for 1 week after the last dose [see Use in Specific Populations (8.3)].
- Advise males with female partners of reproductive potential or who are pregnant to use effective contraception during treatment and for 1 week after receiving the last dose of LYTGOBI [see Use in Specific Populations (8.3)].

Lactation

- Advise patients not to breastfeed during treatment with LYTGOBI and for 1 week after the last dose [see Use in Specific Populations (8.2)].

Administration

- Instruct patients to not crush, chew, split or dissolve tablets.
- Instruct patients if they miss a dose by 12 or more hours or if they vomit after taking a dose, resume dosing with the next scheduled dose. Extra tablets should not be taken to make up for the missed dose [see Dosage and Administration (2.2)].

Drug Interactions

Advise patients to inform their healthcare providers of all concomitant medications, including prescription medicines, over-the-counter drugs, and herbal products. Advise patients to avoid grapefruit products during treatment with LYTGOBI [see Drug Interactions (7.1)].

Manufactured for:
Taiho Pharmaceutical Co., Ltd.
Japan

Distributed by:
Taiho Oncology, Inc.
Princeton, NJ 08540 USA
LYTGOBI is a trademark of Taiho Pharmaceutical Co., Ltd.
U.S. Patent Nos. 9,108,973, 10,434,103, and 11,833,151
© 2025 Taiho Oncology, Inc. All rights reserved

PATIENT INFORMATION
LYTGOBI (light-GOH-bee)
(futibatinib)
tablets

What is LYTGOBI?

LYTGOBI is a prescription medicine that is used to treat adults with bile duct cancer (intrahepatic cholangiocarcinoma) that has spread or cannot be removed by surgery:

- who have already received a previous treatment, and
- whose tumor has a certain type of abnormal "FGFR2” gene.

Your healthcare provider will test your cancer for a certain type of abnormal FGFR2 gene and make sure that LYTGOBI is right for you.
It is not known if LYTGOBI is safe and effective in children.

Before you take LYTGOBI, tell your healthcare provider about all of your medical conditions, including if you:

- have vision or eye problems.
- are pregnant or plan to become pregnant. LYTGOBI can harm your unborn baby or cause loss of your pregnancy (miscarriage). You should not become pregnant during treatment with LYTGOBI.
  Females who can become pregnant:
  - Your healthcare provider should do a pregnancy test before you start treatment with LYTGOBI.
  - You should use an effective method of birth control during treatment and for 1 week after your final dose of LYTGOBI. Talk to your healthcare provider about birth control methods that may be right for you.
  - Tell your healthcare provider right away if you become pregnant or think that you may be pregnant.
    Males with female partners who can become pregnant:
  - You should use effective birth control when sexually active during treatment with LYTGOBI and for 1 week after your last dose of LYTGOBI.
- are breastfeeding or plan to breastfeed. It is not known if LYTGOBI passes into your breast milk. Do not breastfeed during treatment and for 1 week after your last dose of LYTGOBI.

Tell your healthcare provider about all the medicines you take, including prescription and over-the-counter medicines, vitamins, and herbal supplements. LYTGOBI and other medicines may affect each other causing side effects. LYTGOBI may affect the way other medicines work, and other medicines may affect how LYTGOBI works.

How should I take LYTGOBI?

- Take LYTGOBI exactly as your healthcare provider tells you.
- Take LYTGOBI 1 time each day with or without food at about the same time each day. You will continue for as long as your healthcare provider tells you to.
- Swallow LYTGOBI tablets whole. Do not crush, chew, split, or dissolve LYTGOBI tablets. Tell your healthcare provider if you have problems swallowing LYTGOBI tablets whole.
- You should not eat or drink grapefruit products during treatment with LYTGOBI.
- Your healthcare provider may change your dose of LYTGOBI, or may temporarily or completely stop treatment if you get certain side effects.
- If you miss a dose of LYTGOBI, you can take the missed dose within 12 hours on the same day. If more than 12 hours have passed, do not make up the dose. Take your regular dose of LYTGOBI the next day at the usual time. Do not take more LYTGOBI than prescribed to make up for the missed dose.
- If you vomit after taking LYTGOBI, do not take another LYTGOBI tablet. Take your regular dose of LYTGOBI the next day at the usual time.

What are the possible side effects of LYTGOBI?

LYTGOBI may cause serious side effects, including:

- Eye problems. Certain eye problems are common with LYTGOBI but can also be serious. Eye problems include dry eye or inflamed eyes, inflamed cornea (front part of the eye), increased tears, and a disorder of the retina (an internal part of the eye). You will need to see an eye specialist for a complete eye exam before you begin treatment with LYTGOBI, every 2 months for the first 6 months, and every 3 months thereafter during treatment with LYTGOBI.
  - Tell your healthcare provider right away if you develop any changes in your vision during treatment with LYTGOBI, including blurred vision, flashes of light, or seeing black spots. You may need to see an eye specialist right away.
  - You should use artificial tears or substitutes, or hydrating or lubricating eye gels during treatment with LYTGOBI to prevent or treat dry eyes.
- High phosphate levels in your blood (hyperphosphatemia) and build up of minerals in different tissues in your body. Hyperphosphatemia is common with LYTGOBI but can also be serious. High levels of phosphate in your blood may lead to buildup of minerals such as calcium, in different tissues in your body. Your healthcare provider will check your blood phosphate levels during treatment with LYTGOBI.
  - Your healthcare provider may prescribe changes in your diet or phosphate lowering therapy, or change, interrupt or stop LYTGOBI if needed.
  - Tell your healthcare provider right away if you develop any muscle cramps, or numbness or tingling around your mouth.

The most common side effects of LYTGOBI include:

- changes in kidney function blood tests
- increased blood glucose level
- decreased red blood cell, white blood cell, and platelet counts
- increased calcium level in the blood
- decreased sodium and phosphate levels in the blood
- changes in liver function blood tests
- nails separate from the bed or poor formation of the nail; change in the color of nails
- muscle pain
- constipation
- diarrhea
- feeling tired or weak
- changes in tests used to measure your blood clotting time
- dry mouth

- hair loss
- decreased protein level (albumin) in the blood
- mouth sores
- stomach area (abdominal) pain
- dry skin
- decreased glucose and potassium level in the blood
- joint pain
- changes in sense of taste
- dry eye
- nausea
- decrease in appetite
- urinary tract infection
- redness, swelling, peeling or tenderness, mainly on the hands or feet (hand-foot syndrome)
- vomiting

These are not all the possible side effects of LYTGOBI. For more information, ask your healthcare provider or pharmacist.
Call your doctor for medical advice about side effects. You may report side effects to FDA at 1-800-FDA-1088.

How should I store LYTGOBI?

- Store LYTGOBI at room temperature between 68°F to 77°F (20°C to 25°C).

Keep LYTGOBI and all medicines out of the reach of children.

General information about the safe and effective use of LYTGOBI.

Medicines are sometimes prescribed for purposes other than those listed in a Patient Information leaflet. Do not use LYTGOBI for a condition for which it is not prescribed. Do not give LYTGOBI to other people, even if they have the same symptoms you have. It may harm them. If you would like more information, talk with your healthcare provider.
You can ask your pharmacist or healthcare provider for information that is written for healthcare professionals.

What are the ingredients in LYTGOBI?

Active ingredient: futibatinib

Inactive ingredients: corn starch, crospovidone, hydroxypropyl cellulose, lactose monohydrate, magnesium stearate, mannitol, microcrystalline cellulose, and sodium lauryl sulfate.
The film coating material contains: hypromellose, magnesium stearate, polyethylene glycol, and titanium dioxide.

Manufactured for: Taiho Pharmaceutical Co., Ltd. Japan

LYTGOBI is a trademark of Taiho Pharmaceutical Co., Ltd.; U.S. Patent Nos. 9,108,973, 10,434,103, and 11,833,151; © 2025 Taiho Oncology, Inc. All rights reserved
For more information, go to www.LYTGOBI.com or call 1-844-878-2446.

This Patient Information has been approved by the U.S. Food and Drug Administration.

Issued: 7/2025

PRINCIPAL DISPLAY PANEL - Blister 4mg 35ct Card

NDC 64842-0120-6

LYTGOBI®

(futibatinib) tablets

4 mg per tablet

Rx Only

Swallow tablets whole. Do not crush, chew, split, or dissolve.

20 mg daily dose. Take five 4 mg tablets once daily.

TAIHO ONCOLOGY

PRINCIPAL DISPLAY PANEL - Carton 4mg 35ct

NDC 64842-0120-6

Rx Only

LYTGOBI®

(futibatinib) tablets

20 mg daily dose

Take five 4 mg tablets orally once daily

4 mg per tablet
One blister card
containing 35 tablets
7-day supply

TAIHO ONCOLOGY, INC.

PRINCIPAL DISPLAY PANEL - Blister 20mg 14ct Card

NDC 64842-0120-8

TAIHO
ONCOLOGY, INC.

LYTGOBI®
(futibatinib) tablets

20 mg daily dose. Take one 4 mg tablet
and one 16 mg tablet once daily.

Rx Only

Swallow tablets whole. Do not crush, chew, split, or dissolve tablets.

PRINCIPAL DISPLAY PANEL - Carton 20mg 14ct

NDC 64842-0120-8

Rx Only

LYTGOBI®
(futibatinib) tablets

20 mg daily dose

Take one 4 mg tablet and one 16
mg tablet orally once daily

4 mg per tablet (7 tablets)
16 mg per tablet (7 tablets)

Contains: One blister
card containing 14 tablets
7-day supply (14 tablets)

TAIHO
ONCOLOGY, INC.

PRINCIPAL DISPLAY PANEL - Blister 4mg 28ct Card

NDC 64842-0120-5

LYTGOBI®

(futibatinib) tablets

4 mg per tablet

Rx Only

Swallow tablets whole. Do not crush, chew, split, or dissolve.

16 mg daily dose. Take four 4 mg tablets once daily.

TAIHO ONCOLOGY

PRINCIPAL DISPLAY PANEL - Carton 4mg 28ct

NDC 64842-0120-5

Rx Only

LYTGOBI®

(futibatinib) tablets

16 mg daily dose

Take four 4 mg tablets orally once daily

4 mg per tablet
One blister card
containing 28 tablets
7-day supply

TAIHO ONCOLOGY, INC.

PRINCIPAL DISPLAY PANEL - Blister 16mg 7ct Card

NDC 64842-0120-7

TAIHO
ONCOLOGY, INC.

LYTGOBI®
(futibatinib) tablets

16 mg daily dose. Take one
16 mg tablet once daily.

Rx Only

Swallow tablets whole. Do not crush, chew, split, or dissolve tablets.

PRINCIPAL DISPLAY PANEL - Carton 16mg 7ct

NDC 64842-0120-7

Rx Only

LYTGOBI®
(futibatinib) tablets

16 mg daily dose

Take one 16 mg tablet orally once daily

16 mg per tablet

Contains: One blister
card containing 7 tablets
7-day supply (7 tablets)

TAIHO
ONCOLOGY, INC.

PRINCIPAL DISPLAY PANEL - Blister 4mg 21ct Card

NDC 64842-0120-4

LYTGOBI®

(futibatinib) tablets

4 mg per tablet

Rx Only

Swallow tablets whole. Do not crush, chew, split, or dissolve.

12 mg daily dose. Take three 4 mg tablets once daily.

TAIHO ONCOLOGY

PRINCIPAL DISPLAY PANEL - Carton 4mg 21ct

NDC 64842-0120-4

Rx Only

LYTGOBI®

(futibatinib) tablets

12 mg daily dose

Take three 4 mg tablets orally once daily

4 mg per tablet
One blister card
containing 21 tablets
7-day supply

TAIHO ONCOLOGY, INC.